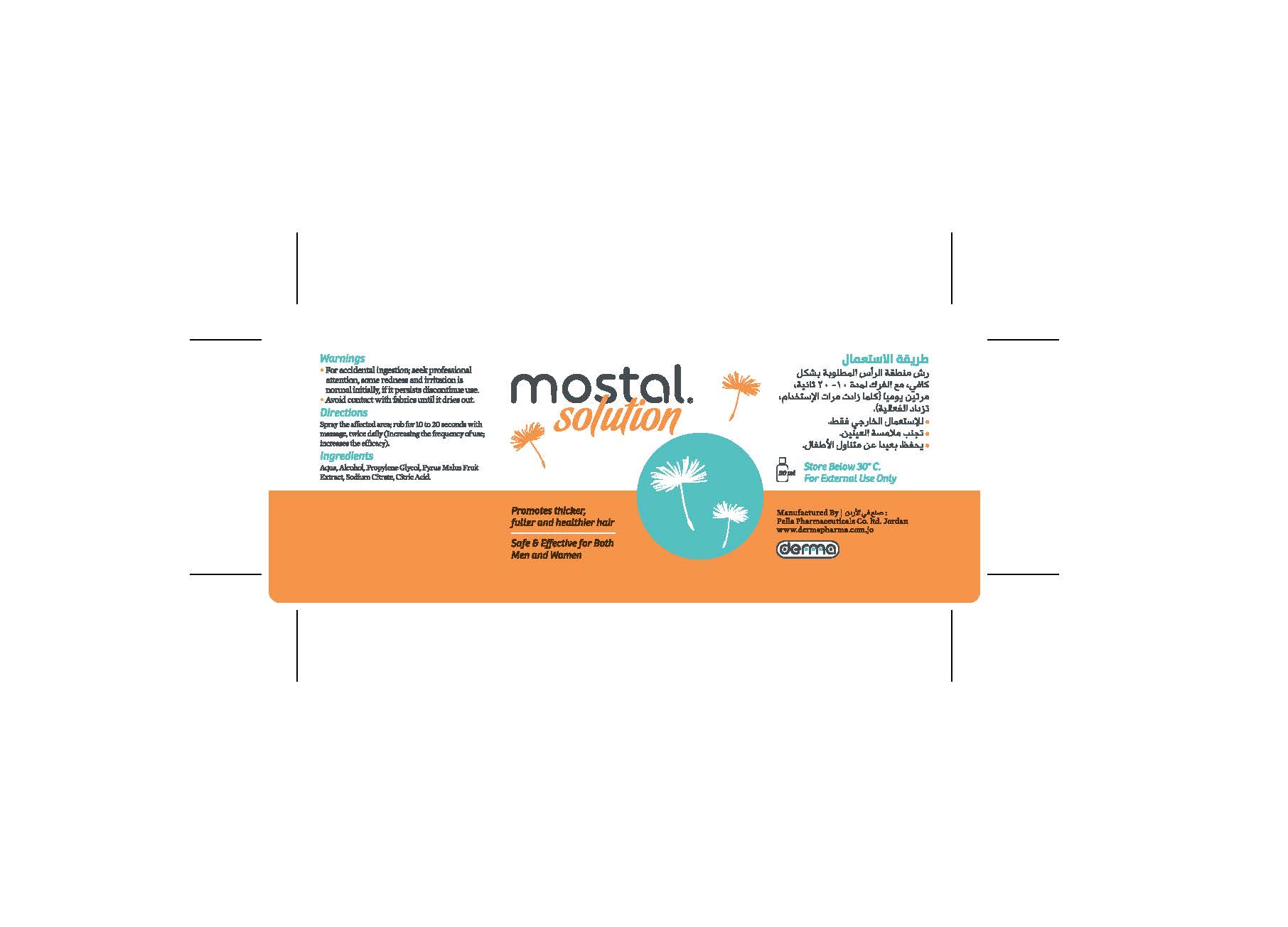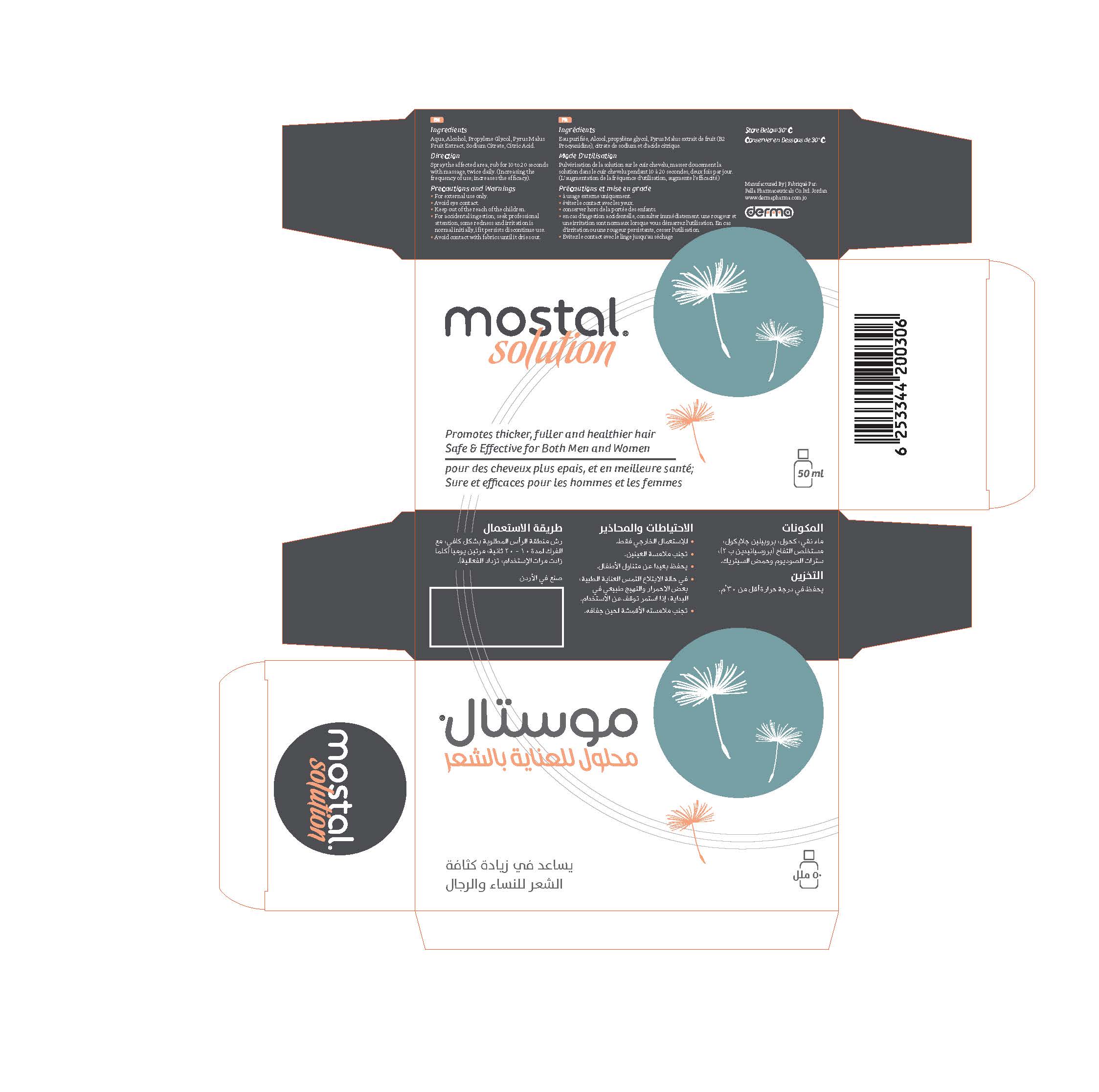 DRUG LABEL: Mostal
NDC: 82160-306 | Form: SOLUTION
Manufacturer: Pella Pharmaceuticals Co. Ltd
Category: otc | Type: HUMAN OTC DRUG LABEL
Date: 20241231

ACTIVE INGREDIENTS: APPLE 500 mg/50 mL
INACTIVE INGREDIENTS: ANHYDROUS CITRIC ACID; PROPYLENE GLYCOL; ALCOHOL; WATER; SODIUM CITRATE

Mostal

Forms and presentation

Topical Solution: Bottle of 50 ml.

Active Ingredient

Pyrus Malus (Apple) Fruit Extract (Procyanidine B2)

Inactive Ingredients

Aqua, Alcohol, Propylene Glycol, Sodium Citrate, Citric Acid.

Purpose

Hair growth enhancer

Properties

Mostal® solution that helps to stop hair fall; improves hair growth and increases its density.

Indications

Mostal® solution is recommended for men and women to stop hair fall; improves hair growth and increases its density.

Precautions

Keep out of reach of children

Warnings

- For external use only
- Avoid eye contact
- For accidental ingestion; seek professional attention, some redness and irritation is normal initially, if it persists discontinue use
- Avoid contact with fabrics until it dries out

Contraindications

Hypersensitivity to any of the components.

Side effects

Mostal® solution has no known side effect, the use of it is without risk.

Dosage and administration

Spraying the solution on the scalp, the solution gently massaged into the scalp for 10 to 20 seconds, twice daily.
The increase in frequency of use, increases efficiency.

Storage conditions

Store at a temperature below 30 ° C.